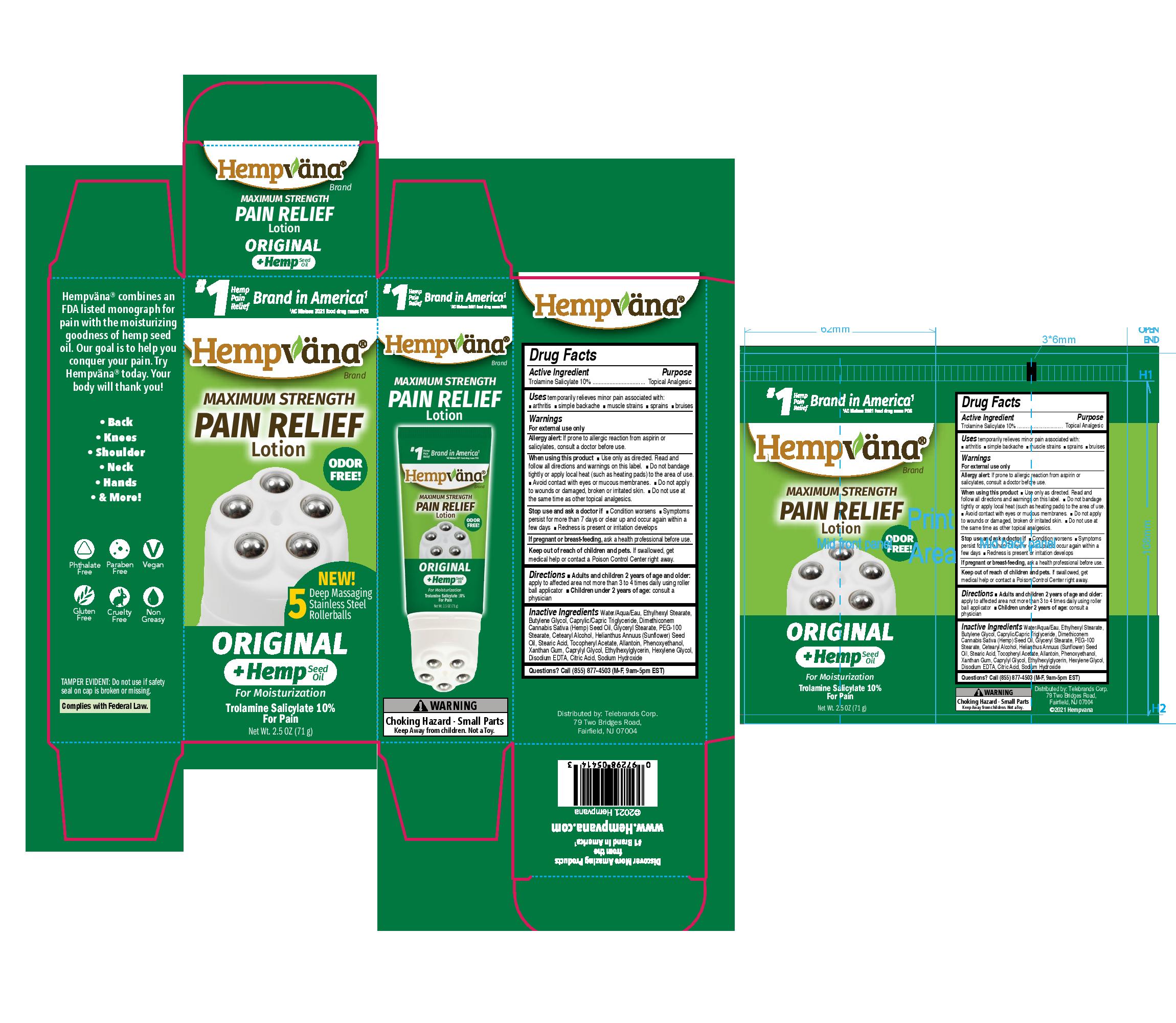 DRUG LABEL: Hempvana Maximum Strength Pain Relief
NDC: 73287-022 | Form: LOTION
Manufacturer: TELEBRANDS CORP
Category: otc | Type: HUMAN OTC DRUG LABEL
Date: 20241120

ACTIVE INGREDIENTS: TROLAMINE SALICYLATE 10 g/100 g
INACTIVE INGREDIENTS: EDETATE DISODIUM ANHYDROUS; CITRIC ACID MONOHYDRATE; SODIUM HYDROXIDE; CETOSTEARYL ALCOHOL; SUNFLOWER OIL; WATER; ETHYLHEXYL STEARATE; BUTYLENE GLYCOL; .ALPHA.-TOCOPHEROL ACETATE; PHENOXYETHANOL; ETHYLHEXYLGLYCERIN; PEG-100 STEARATE; STEARIC ACID; ALLANTOIN; XANTHAN GUM; CAPRYLYL GLYCOL; HEXYLENE GLYCOL; DIMETHICONE; CANNABIS SATIVA SEED OIL; GLYCERYL MONOSTEARATE; MEDIUM-CHAIN TRIGLYCERIDES

Hempvana Rollerballs (Original)

Active Ingredient

Trolamine Salicylate 10%

Purpose

Trolamine Salicylate 10%..................Topical Analgesic

Uses

temporarily relieves minor pain associated with:

- arthritis
- simple backache
- muscle strains
- sprains
- bruises

Warnings

For external use only

Allergy alert:If prone to allergic reaction from aspirin or salicylates, consult a doctor before use.

When using this product

- Use only as directed. Read and follow all directions and warnings on this label.
- Do not bandage tightly or apply local heat (such as heating pads) to the area of use.
- Avoid contact with eyes or mucous membranes.
- Do not apply to wounds or damaged, broken, or irritated skin.
- Do not use at the same time as other topical analgesics.

Stop use and ask a doctor if

- Condition worsens
- Symptoms persist for more than 7 days or clear up and occur again within a few days
- Redness is present or irritation develops

PREGNANCY OR BREAST FEEDING

If pregnant or breast-feeding,ask a health professional before use.

Keep out of reach of children and pets.If swallowed, get medical help or contact a Poison Control Center right away.

Directions

- Adults and children 2 years of age and older:apply to affected area not more than 3 to 4 times daily using roller ball applicator
- Children under 2 years of age:consult a physician

Inactive Ingredients

Water/Aqua/Eau, Ethylhexyl Stearate, Butylene Glycol, Caprylic/Capric Triglyceride, Dimethicone, Cannabis Sativa (Hemp) Seed Oil, Glyceryl Stearate, PEG-100 Stearate, Cetearyl Alcohol, Helianthus Annuus (Sunflower) Seed Oil, Stearic Acid, Tocopheryl Acetate, Allantoin, Phenoxyethanol, Xanthan Gum, Caprylyl Glycol, Ethylhexylglycerin, Hexylene Glycol, Disodium EDTA, Citric Acid, Sodium Hydroxide

Questions?

Call (855) 877-4503 (M-F, 9am-5pm EST)

PACKAGE LABEL

#1 Hemp Pain Relief Brand in America^1

^1AC Nielsen 2021 food drug mass POS

Hempvana Brand

Maximum Strength Pain Relief Lotion

Odor Free!

New! 5 Deep Massaging Stainless Steel Rollerballs

Original

+Hemp Seed Oil

For Moisturization

Trolamine Salicylate 10% For Pain

Net Wt. 2.5 OZ (71 g)